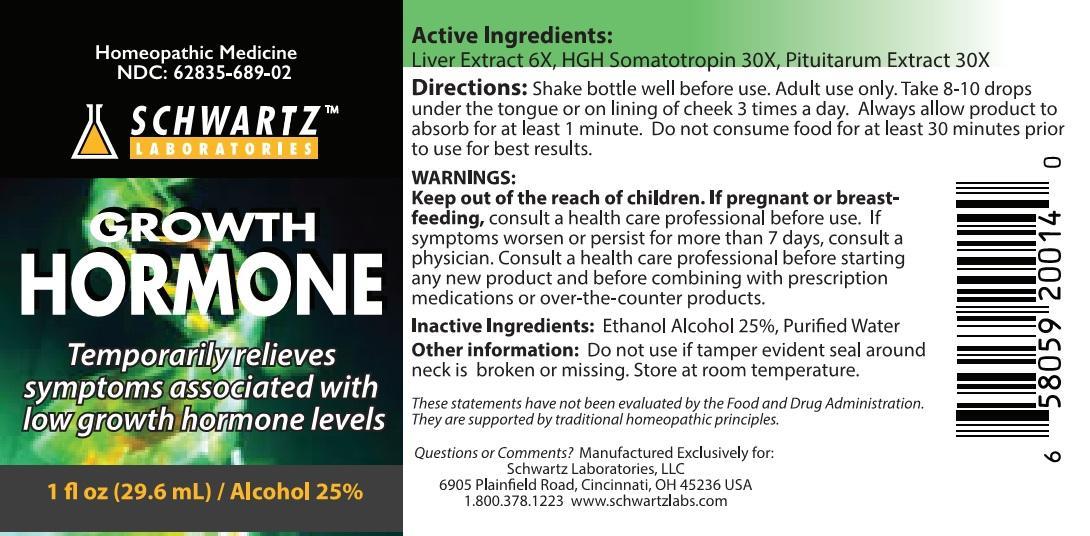 DRUG LABEL: Growth Hormone
                
NDC: 62835-689 | Form: LIQUID
Manufacturer: Midlink LLC
Category: homeopathic | Type: HUMAN OTC DRUG LABEL
Date: 20140506

ACTIVE INGREDIENTS: PORK LIVER 6 [hp_X]/1 mL; SOMATROPIN 30 [hp_X]/1 mL; SUS SCROFA PITUITARY GLAND 30 [hp_X]/1 mL
INACTIVE INGREDIENTS: ALCOHOL; WATER

Schwartz Laboratories GROWTH HORMONE

Active Ingredients:

Liver Extract 6X, HGH Somatotropin 30X, Pituitarum Extract 30X

Directions:

Shake bottle well before use. Adult use only. Take 8-10 drops under the tongue or on lining of cheek 3 times a day. Always allow product to absorb for at least 1 minute. Do not consume food for at least 30 minutes prior to use for best results.

WARNINGS:

Keep out of the reach of children. If pregnant or breast-feeding, consult a health care professional before use. If symptoms worsen or persist for more than 7 days, consult a physician. Consult a health care professional before starting any new product and before combining with prescription medications or over-the-counter products.

Keep out of the reach of children.

INDICATIONS AND USAGE

Temporarily relieves symptoms associated with low growth hormone levels.

Inactive Ingredients: Ethanol Alcohol 25%, Purified Water.

Other information: Do not use if tamper evident seal around neck is broken or missing. Store at room temperature.

These statements have not been evaluated by the Food and Drug Administration. They are supported by traditional homeopathic principles.

Questions or Comments?

Manufactured Exclusively for:

Schwartz Laboratories, LLC

6905 Plainfield Road, Cincinnati, OH 45236 USA

1.800.378.1223 www.schwartzlabs.com

PACKAGE LABEL

HOMEOPATHIC MEDICINE

NDC: 62835-689-02

SCHWARTZ LABORATORIES

GROWTH HORMONE

Temporarily relieves symptoms associated with low growth hormone levels

1 fl oz (29.6 mL) / Alcohol 25%

PURPOSE

Temporarily relieves symptoms associated with low growth hormone levels